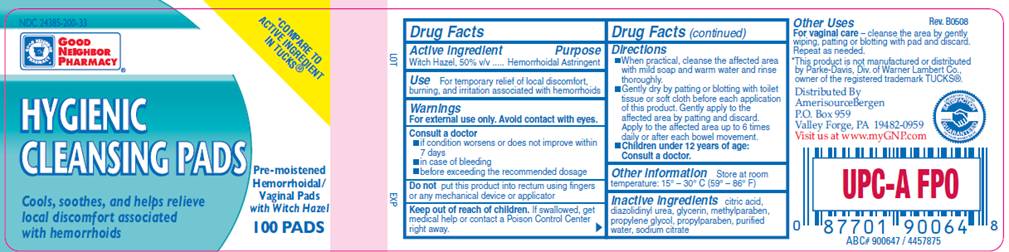 DRUG LABEL: Hygienic Cleansing Pads
NDC: 24385-200 | Form: SOLUTION
Manufacturer: Amerisource Bergen
Category: otc | Type: HUMAN OTC DRUG LABEL
Date: 20100104

ACTIVE INGREDIENTS: witch hazel 0.50 mL/1 mL
INACTIVE INGREDIENTS: citric acid monohydrate; diazolidinylurea; glycerin; methylparaben; propylene glycol; propylparaben; sodium citrate; water

DRUG FACTS

ACTIVE INGREDIENT

Witch Hazel 50% v/v

PURPOSE

Hemorrhoidal Astringent

USE

For temporary relief of local discomfort, burning, and irritation associated with hemorrhoids

WARNINGS

For external use only. Avoid contact with eyes.

Consult a doctor

- if condition worsens or does not improve within 7 days
- in case of bleeding
- before exceeding the recommended dosage

Do not

put this product into rectum using fingers or any mechanical device or applicator

Keep out of reach of children

If swallowed, get medical help or contact a Poison Control Center right away.

DIRECTIONS

- When practical, cleanse the affected area with mild soap and warm water and rinse thoroughly.
- Gently dry by patting or blotting with toilet tissue or soft cloth before each application of this product. Gently apply to the affected area by patting and then discard. Apply to the affected area up to 6 times daily or after each bowel movement.
- Children under 12 years of age: consult a doctor.

OTHER INFORMATION

Store at room temperature: 15°- 30° C (59° - 86° F)

OTHER USES

For vaginal care - cleanse the area by gently wiping, patting or blotting with pad and discard. Repeat as needed.

INACTIVE INGREDIENTS

citric acid, diazolidinyl urea, glycerin, methylparaben, propylene glycol, propylparaben, purified water, sodium citrate

PACKAGE INFORMATION

NDC 24385-200-33

GOOD NEIGHBOR PHARMACY
*COMPARE TO ACTIVE INGREDIENT IN TUCKS®
HYGIENIC
CLEANSING PADS
Pre-moistened Hemorrhoidal/Vaginal Pads with Witch Hazel
100 PADS
Cools, soothes, and helps relieve local discomfort associated with hemorrhoids
*This product is not manufactured or distributed by Parke-Davis, Div. of Warner Lambert Co., owner of the registered trademark TUCKS®.
Distributed by AmerisourceBergen
P.O. Box 959
Valley Forge, PA 19482-0959
Visit us at www.myGNP.com